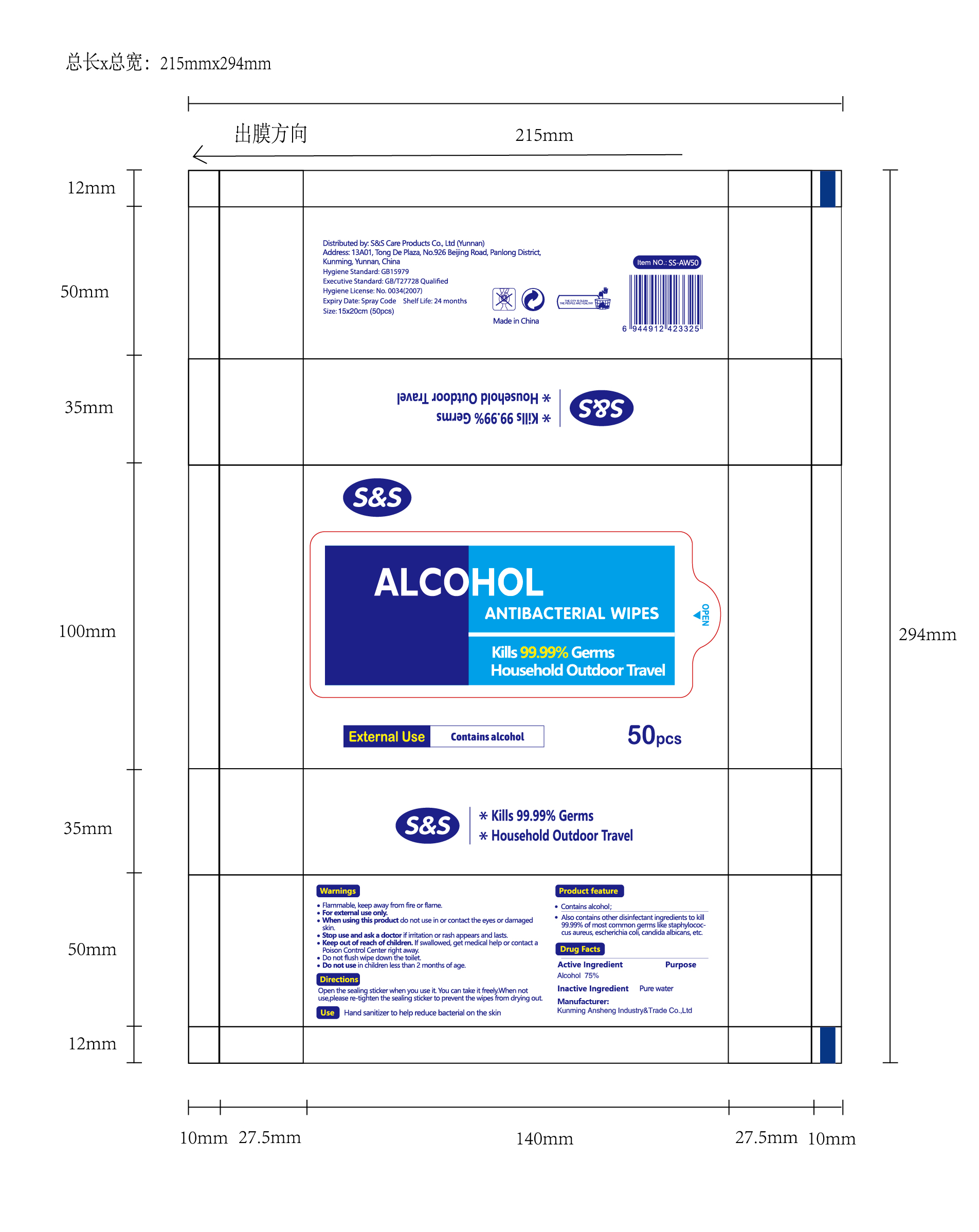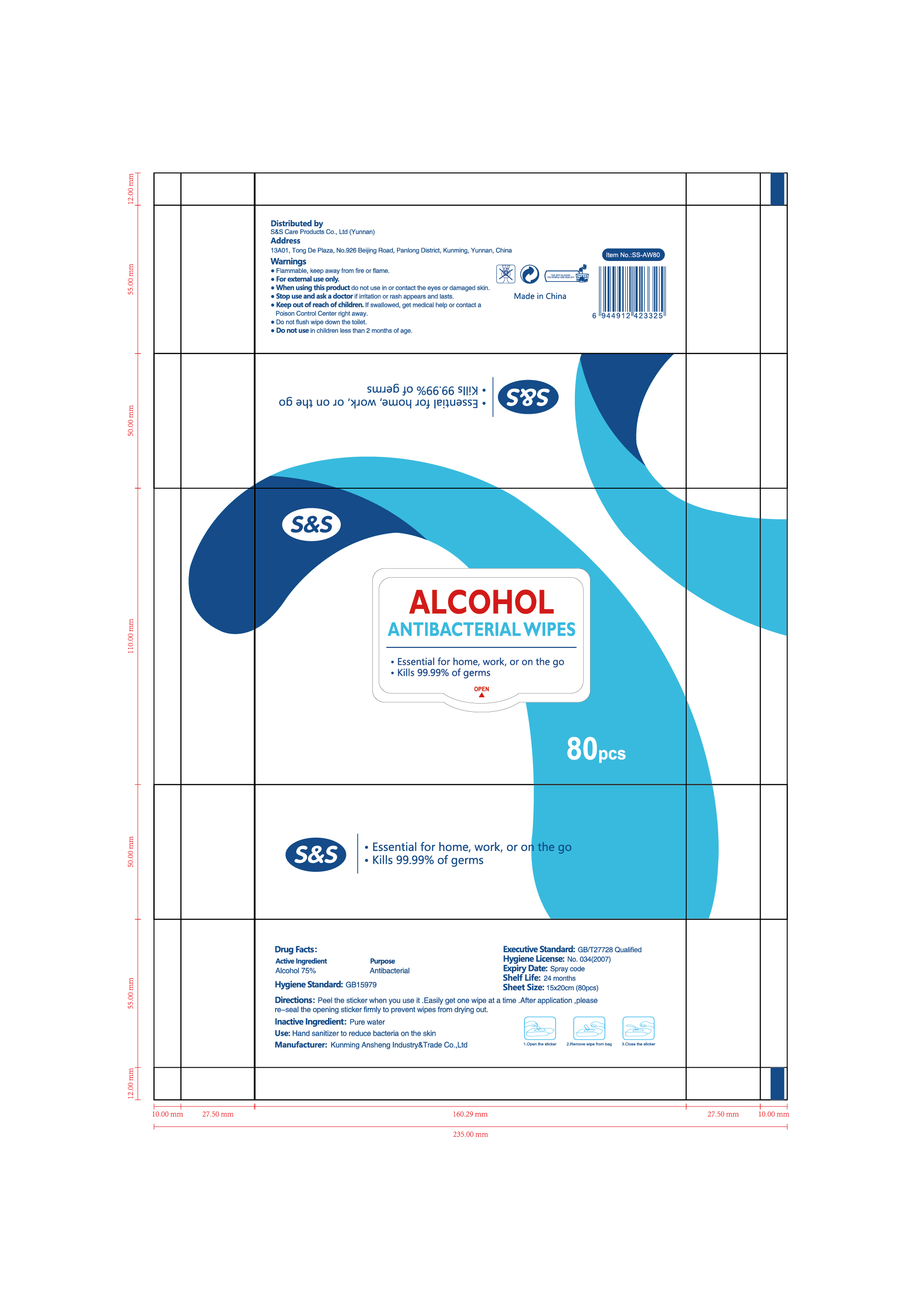 DRUG LABEL: Alcohol Antibacterial Wipes
NDC: 78183-015 | Form: CLOTH
Manufacturer: Kunming Ansheng Industry & Trade Co., Ltd.
Category: otc | Type: HUMAN OTC DRUG LABEL
Date: 20200603

ACTIVE INGREDIENTS: CHLORHEXIDINE ACETATE 0.1 g/100 a; BENZALKONIUM CHLORIDE 0.1 g/100 a; ALCOHOL 15 g/100 a
INACTIVE INGREDIENTS: WATER

Alcohol Antibacterial Wipes

Active Ingredient(s)

ethanol15.0%

Chlorhexidine diacetate0.1%

Benzalkonium chloride0.1%

Purpose

Antibacterial

Use

Hand Sanitizer to reduce bacteria on the skin

Warnings

Flammable. Keep away from heat or flame

do not use in or contact the eyes or damaged skin

Do not use

- in children less than 2 months of age
- on open skin wounds

Stop use and ask a doctor if irritation or rash appears and lasts

Keep out of reach of children. If swallowed, get medical help or contact a Poison Control Center right away.

Directions

peel the sticker when you use it. Easily get one wipe at a time. After application, please re-seal the opening sticker firmly to prevent wipes from drying out

Inactive ingredients

pure water